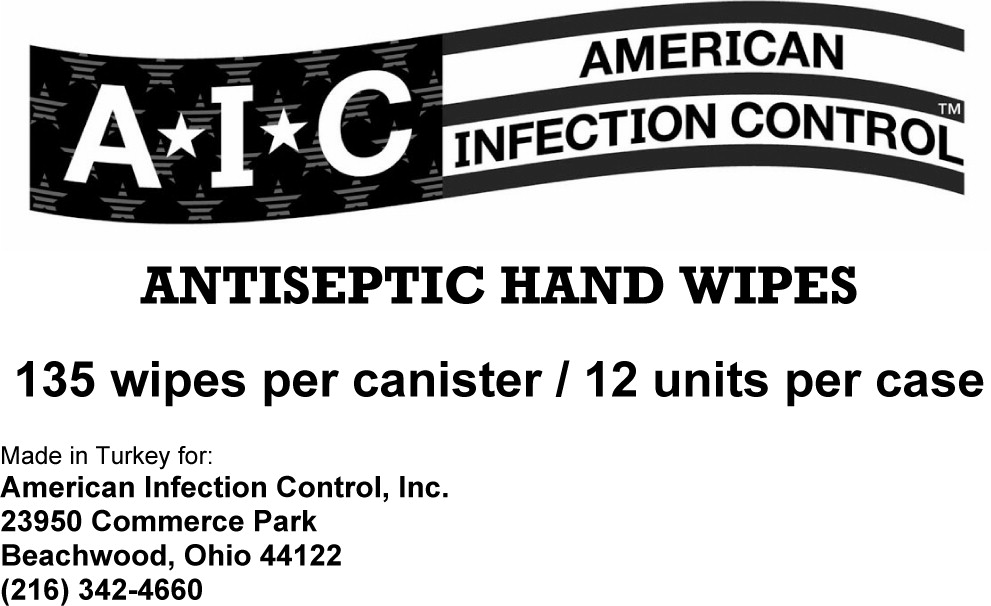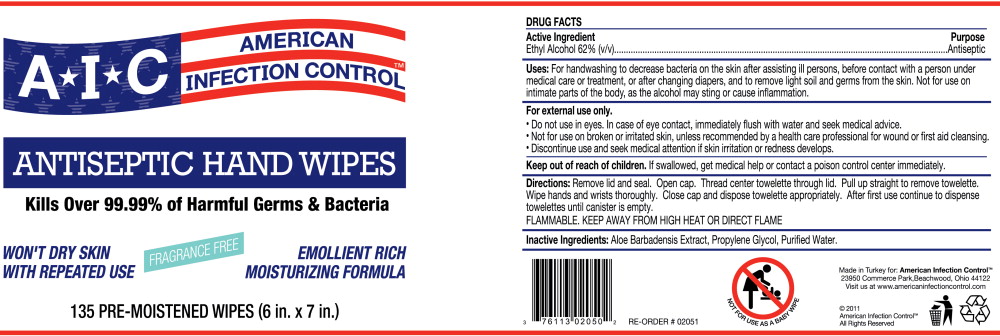 DRUG LABEL: American Infection Control Antiseptic Hand Wipes
NDC: 76113-012 | Form: CLOTH
Manufacturer: American Infection Control, Inc.
Category: otc | Type: HUMAN OTC DRUG LABEL
Date: 20120206

ACTIVE INGREDIENTS: Alcohol .62 mL/1 mL
INACTIVE INGREDIENTS: Aloe Vera Leaf; Propylene Glycol; Water

DRUG FACTS

Active Ingredient

Ethyl Alcohol 62% (v/v)

Purpose

Antiseptic

Uses:

For handwashing to decrease bacteria on the skin after assisting ill persons, before contact with a person under medical care or treatment, or after changing diapers, and to remove light soil and germs from the skin. Not for use on intimate parts of the body, as the alcohol may sting or cause inflammation.

WARNINGS

For external use only.

- Do not use in eyes. In case of eye contact, immediately flush with water and seek medical advice.
- Not for use on broken or irritated skin, unless recommended by a health care professional for wound or first aid cleansing.
- Discontinue use and seek medical attention if skin irritation or redness develops.

Keep out of reach of children. If swallowed, get medical help or contact a poison control center immediately.

Directions:

Remove lid and seal. Open cap. Thread center towelette through lid. Pull up straight to remove towelette. Wipe hands and wrists thoroughly. Close cap and dispose towelette appropriately. After first use continue to dispense towelettes until canister is empty.

FLAMMABLE. KEEP AWAY FROM HIGH HEAT OR DIRECT FLAME

Inactive Ingredients:

Aloe Barbadensis Extract, Propylene Glycol, Purified Water.

Principal Display Panel – Case Label

A I C AMERICAN INFECTION CONTROL™

ANTISEPTIC HAND WIPES
135 wipes per canister / 12 units per case

Made in Turkey for:
American Infection Control, Inc.
23950 Commerce Park
Beachwood, Ohio 44122
(216) 342-4660

Principal Display Panel – Canister Label

A I C AMERCIAN INFECTION CONTROL

ANTISEPTIC HAND WIPES
Kills Over 99.99% of Harmful Germs & Bacteria

WON'T DRY SKIN FRAGRANCE FREE EMOLLIENT RICH
WITH REPEATED USE MOISTURIZING FORMULA

135 PRE-MOISTENED WIPES (6 in. x 7 in.)